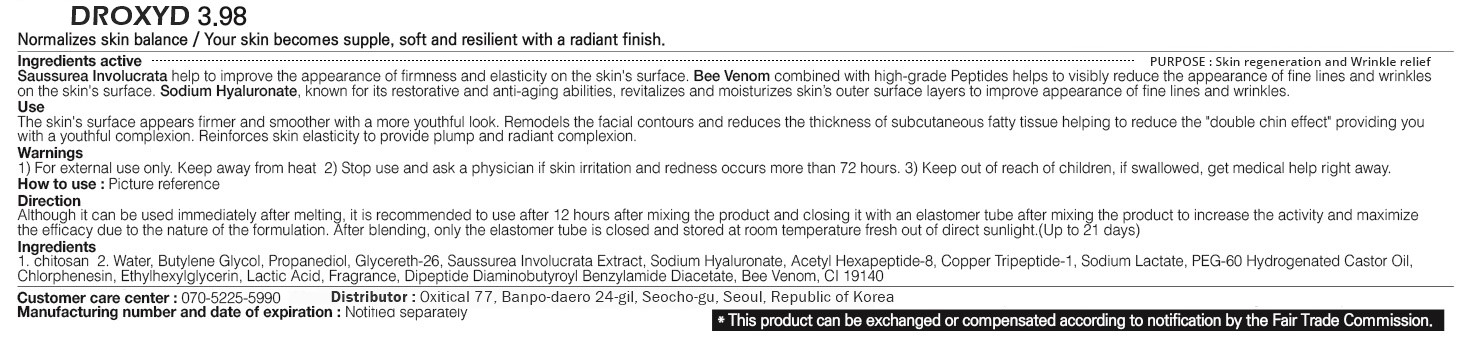 DRUG LABEL: DROXYD 3.98
NDC: 80851-403 | Form: LIQUID
Manufacturer: Oxytical
Category: otc | Type: HUMAN OTC DRUG LABEL
Date: 20231228

ACTIVE INGREDIENTS: CHITOSAN MEDIUM MOLECULAR WEIGHT (200-400 MPA.S) 99.99 mg/100 mL
INACTIVE INGREDIENTS: WATER 0.001 mL/100 mL

Active Ingredients

Chitosan

Purpose

Skin regeneration and Wrinkle relief

Use

The skin's surface appears firmer and smoother with a more youthful look. Remodels the facial contours and reduces the thickness of subcutaneous fatty tissue helping to reduce the "double chin effect" providing you with a youthful complexion. Reinforces skin elasticity to provide plump and radiant complexion.

Directions

[Preparation stage]

After cleansing, use toner to clean up the skin.

It must be used only after cleansing is complete, and especially pay attention to the cleanliness of your hands.

If you use it after exfoliation, you can get more satisfactory results, and it is more effective if you give a simple massage before use.

[Application stage]

1. Prepare Core peptide(1st), Stable Chitin(2nd) and a syringe.

2. Core Peptide(1st) only opens the plastic cap.

3. A syringe inlet is injected into the center of the hole at the top of the Core Peptide(1st) to suction. (Total 3ml based on syringe).

After the syringe is removed, the inlet is automatically sealed to prevent outside air from entering.

4. Open the Stable Chitin(2nd) after referring to the precautions and inject the Core Peptide(1st).

Due to the nature of the Stable Chitin component, it is not soluble in ampoule other than Core Peptide. (Not compatible)

5. Close the vial opening of the Stable Chitin(2nd) with an elastomer tube and shake to dissolve the Stable Chitin.

Check with eyes and if the Stable Chitin component does not appear in the form of a thread (slightly thick), apply it to the skin.

When Using

Although it can be used immediately after melting, it is recommended to use after 12 hours after mixing the product and closing it with an elastomer tube after mixing the product to increase the activity and maximize the efficacy due to the nature of the formulation.

After blending, only the elastomer tube is closed and stored at room temperature fresh out of direct sunlight.

(Up to 21 days)

Ingredient

Chitosan

Warnings

For external use only.

Keep away from heat.

Stop Using

Stop use and ask a physician if skin irritation and redness occurs more that 72 hours.

Keep out of reach of children, if swallowed, get medical help right away.

Package Label

OXITICAL